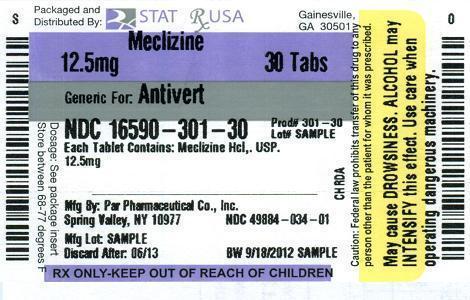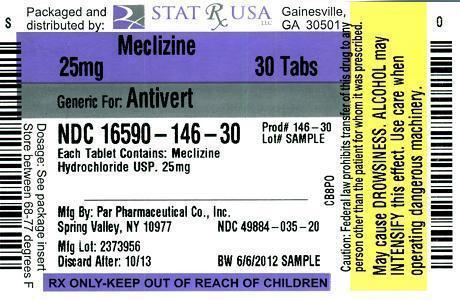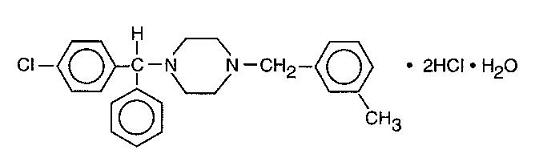 DRUG LABEL: MECLIZINE HYDROCHLORIDE
                
NDC: 16590-301 | Form: TABLET
Manufacturer: STAT Rx USA LLC
Category: prescription | Type: HUMAN PRESCRIPTION DRUG LABEL
Date: 20120920

ACTIVE INGREDIENTS: MECLIZINE HYDROCHLORIDE 12.5 mg/1 1
INACTIVE INGREDIENTS: ANHYDROUS LACTOSE; CELLULOSE, MICROCRYSTALLINE; SODIUM STARCH GLYCOLATE TYPE A POTATO; STARCH, CORN; STEARIC ACID; WATER; ISOPROPYL ALCOHOL; FD&C BLUE NO. 1; MAGNESIUM STEARATE; COLLOIDAL SILICON DIOXIDE

DESCRIPTION

Meclizine hydrochloride, an oral antiemetic, is a white, slightly yellowish, crystalline powder which has a slight odor and is tasteless. It has the following structural formula:

C25H27CIN2•2HCI•H2O M.W. 481.89

The chemical name is 1-(p-chloro-alpha-phenylbenzyl)-4-(m-methyl-benzyl) - piperazine dihydrochloride monohydrate.

Meclizine Hydrochloride Tablets are available in 12.5 mg, and *25 mg strengths for oral administration.

*Contains FD&C Yellow #5 (see PRECAUTIONS).

Each tablet contains the following inactive ingredients: colloidal silicon dioxide, lactose, magnesium stearate, microcrystalline cellulose, sodium starch glycolate, starch, and stearic acid. In addition, the 12.5 mg tablet contains FD&C Blue #1; and the 25 mg tablet contains D&C Yellow #10 and FD&C Yellow #5.

CLINICAL PHARMACOLOGY

Meclizine hydrochloride is an antihistamine which shows marked protective activity against nebulized histamine and lethal doses of intravenously injected histamine in guinea pigs. It has a marked effect in blocking the vasodepressor response to histamine, but only a slight blocking action against acetylcholine. Its activity is relatively weak in inhibiting the spasmogenic action of histamine on isolated guinea pig ileum.

INDICATIONS AND USAGE

For the prevention and treatment of nausea, vomiting, or dizziness associated with motion sickness.

CONTRAINDICATIONS

Meclizine hydrochloride is contraindicated in individuals who have shown a previous hypersensitivity to it.

WARNINGS

Since drowsiness may, on occasion, occur with use of this drug, patients should be warned of this possibility and cautioned against driving a car or operating dangerous machinery.

Patients should avoid alcoholic beverages while taking the drug. Due to its potential anticholinergic action, this drug should be used with caution in patients with asthma, glaucoma, or enlargement of the prostate gland. Do not give to children under 12 years of age unless directed by a doctor.

PRECAUTIONS

The Meclizine Hydrochloride Tablets, 25 mg contain FD&C Yellow #5 (tartrazine) which may cause allergic-type reactions (including bronchial asthma) in certain susceptible individuals. Although the overall incidence of FD&C Yellow #5 (tartrazine) sensitivity in the general population is low, it is frequently seen in patients who also have aspirin hypersensitivity.

Usage in Children: Clinical studies establishing safety and effectiveness in children have not been done; therefore, usage is not recommended under 12 years of age.

Usage in Pregnancy: Pregnancy Category B. Reproduction studies in rats have shown cleft palates at 25-50 times the human dose. Epidemiological studies in pregnant women, however, do not indicate that meclizine hydrochloride increases the risk of abnormalities when administered during pregnancy.

Despite the animal findings, it would appear that the possibility of fetal harm is remote. Nevertheless, meclizine hydrochloride, or any other medication should be used during pregnancy only if clearly necessary.

ADVERSE REACTIONS

Drowsiness, dry mouth, and on rare occasions, blurred vision have been reported.

DOSAGE AND ADMINISTRATION

Motion Sickness: The initial dose of 25 to 50 mg meclizine hydrochloride, should be taken one hour prior to travel for protection against motion sickness. Thereafter, the dose may be repeated every 24 hours for the duration of the journey.

HOW SUPPLIED

Meclizine Hydrochloride Tablets, USP 12.5 mg - blue, oval tablets debossed with "034" on one side and "par" on the other side. Tablets may contain characteristic dye spots. They are supplied in:

Bottles of 30 NDC 16590-301-30

Bottles of 60 NDC 16590-301-60

Bottles of 90 NDC 16590-301-90

Meclizine Hydrochloride Tablets, USP 25 mg - yellow, oval tablets debossed with “035” on one side and “par” on the other side. They are supplied in:

Bottles of 14 NDC 16590-146-14

Bottles of 15 NDC 16590-146-15

Bottles of 20 NDC 16590-146-20

Bottles of 30 NDC 16590-146-30

Bottles of 40 NDC 16590-146-40

Bottles of 60 NDC 16590-146-60

Bottles of 90 NDC 16590-146-90

Dispense in tight, light-resistant containers as defined in the USP.

Store at controlled room temperature 15°-30°C (59°-86°F).

Manufactured by:

PAR PHARMACEUTICAL COMPANIES, INC.

Spring Valley, NY 10977

Revised: 11/09

OS034-01-1-11

Relabeling and Repackaging by:
STAT Rx USA LLC
Gainesville, GA